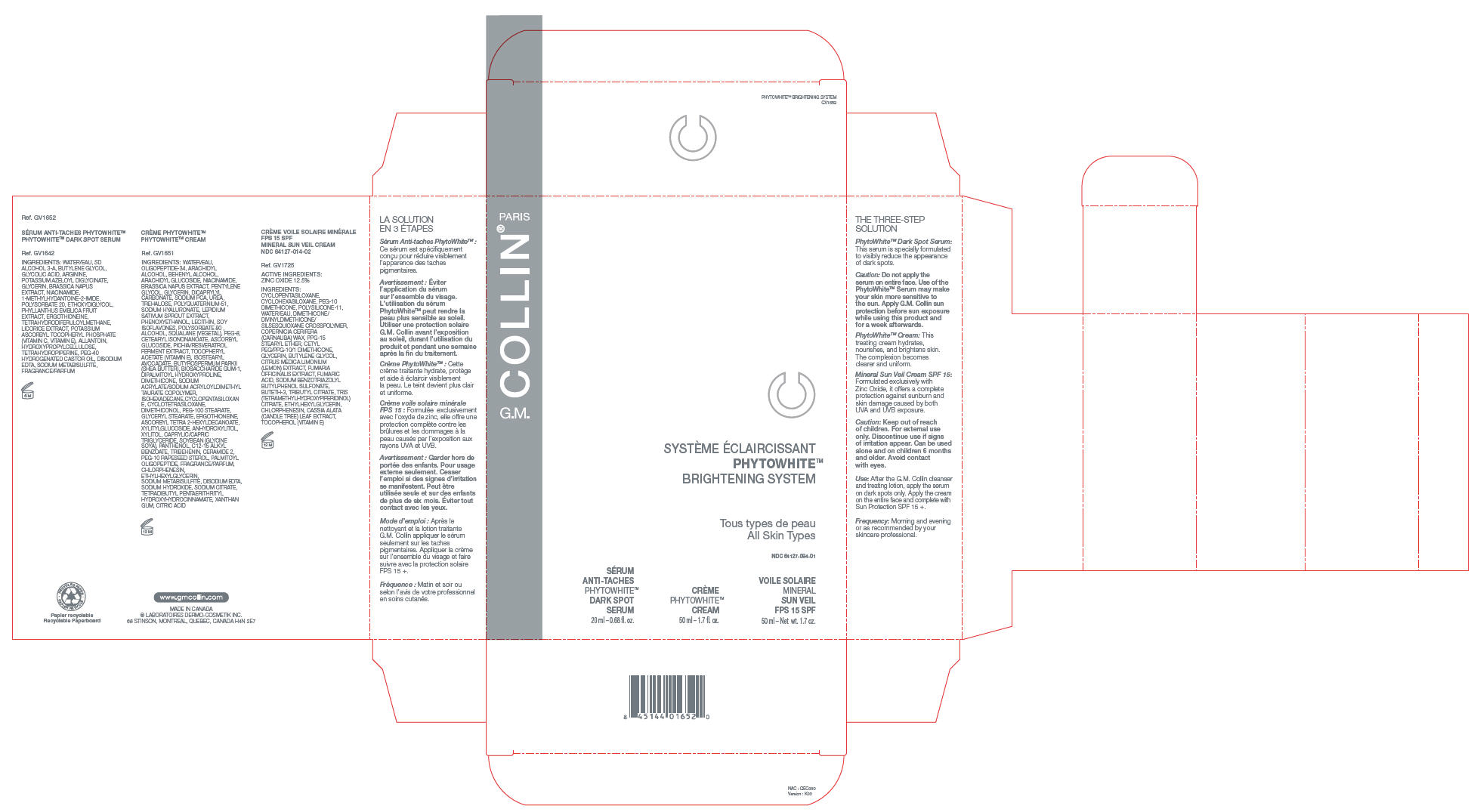 DRUG LABEL: G.M. Collin Mineral Sun Veil
NDC: 64127-084 | Form: CREAM
Manufacturer: Laboratoires Dermo Cosmetik Inc.
Category: otc | Type: HUMAN OTC DRUG LABEL
Date: 20100512

ACTIVE INGREDIENTS: zinc oxide 0.125 mL/1 mL
INACTIVE INGREDIENTS: CYCLOMETHICONE 5; CYCLOMETHICONE 6; WATER; CARNAUBA WAX; GLYCERIN; BUTYLENE GLYCOL; LEMON; FUMARIC ACID; ETHYLHEXYLGLYCERIN; CHLORPHENESIN; ALPHA-TOCOPHEROL

PHYTOWHITE™
BRIGHTENING SYSTEM

THE THREE-STEP SOLUTION

PhytoWhite™ Dark Spot Serum

This serum is specially formulated to visibly reduce the appearance of dark spots.

Caution: Do not apply the serum on entire face. Use of the PhytoWhite™ Serum may make your skin more sensitive to the sun. Apply G.M. Collin sun protection before sun exposure while using this product and for a week afterwards.

PhytoWhite™ Cream: This treating cream hydrates, nourishes, and brightens skin. The complexion becomes clearer and uniform.

Mineral Sun Veil Cream SPF 15: Formulated exclusively with Zinc Oxide, it offers a complete protection against sunburn and skin damage caused by both UVA and UVB exposure.

Caution: Keep out of reach of children. For external use only. Discontinue use if signs of irritation appear. Can be used alone and on children 6 months and older. Avoid contact with eyes.

Use: After the G.M. Collin cleanser and treating lotion, apply the serum on dark spots only. Apply the cream on the entire face and complete with Sun Protection SPF 15 +.

Frequency: Morning and evening or as recommended by your skincare professional.

Ref. GV1652

PHYTOWHITE™ DARK SPOT SERUM

Ref. GV1642

INGREDIENTS

WATER/EAU, SD ALCOHOL 3-A, BUTYLENE GLYCOL, GLYCOLIC ACID, ARGININE, POTASSIUM AZELOYL DIGLYCINATE, GLYCERIN, BRASSICA NAPUS EXTRACT, NIACINAMIDE, 1-METHYLHYDANTOINE-2-IMIDE, POLYSORBATE 20, ETHOXYDIGLYCOL, PHYLLANTHUS EMBLICA FRUIT EXTRACT, ERGOTHIONEINE, TETRAHYDRODIFERULOYLMETHANE, LICORICE EXTRACT, POTASSIUM ASCORBYL TOCOPHERYL PHOSPHATE (VITAMIN C, VITAMIN E), ALLANTOIN, HYDROXYPROPYLCELLULOSE, TETRAHYDROPIPERINE, PEG-40 HYDROGENATED CASTOR OIL, DISODIUM EDTA, SODIUM METABISULFITE, FRAGRANCE/PARFUM

PHYTOWHITE™ CREAM

Ref. GV1651

INGREDIENTS

WATER/EAU, OLIGOPEPTIDE-34, ARACHIDYL ALCOHOL, BEHENYL ALCOHOL, ARACHIDYL GLUCOSIDE, NIACINAMIDE, BRASSICA NAPUS EXTRACT, PENTYLENE GLYCOL, GLYCERIN, DICAPRYLYL CARBONATE, SODIUM PCA, UREA, TREHALOSE, POLYQUATERNIUM-51, SODIUM HYALURONATE, LEPIDIUM SATIVUM SPROUT EXTRACT, PHENOXYETHANOL, LECITHIN, SOY ISOFLAVONES, POLYSORBATE 80 , ALCOHOL, SQUALANE (VEGETAL), PEG-8, CETEARYL ISONONANOATE, ASCORBYL GLUCOSIDE, PICHIA/RESVERATROL FERMENT EXTRACT, TOCOPHERYL ACETATE (VITAMIN E), ISOSTEARYL AVOCADATE, BUTYROSPERMUM PARKII (SHEA BUTTER), BIOSACCHARIDE GUM-1, DIPALMITOYL HYDROXYPROLINE, DIMETHICONE, SODIUM ACRYLATE/SODIUM ACRYLOYLDIMETHYL TAURATE COPOLYMER, ISOHEXADECANE,CYCLOPENTASILOXAN E, CYCLOTETRASILOXANE, DIMETHICONOL, PEG-100 STEARATE, GLYCERYL STEARATE, ERGOTHIONEINE, ASCORBYL TETRA 2-HEXYLDECANOATE, XYLITYLGLUCOSIDE, ANHYDROXYLITOL, XYLITOL, CAPRYLIC/CAPRIC TRIGLYCERIDE, SOYBEAN (GLYCINE SOYA), PANTHENOL, C12-15 ALKYL BENZOATE, TRIBEHENIN, CERAMIDE 2, PEG-10 RAPESEED STEROL, PALMITOYL OLIGOPEPTIDE, FRAGRANCE/PARFUM, CHLORPHENESIN, ETHYLHEXYLGLYCERIN, SODIUM METABISULFITE, DISODIUM EDTA, SODIUM HYDROXIDE, SODIUM CITRATE, TETRADIBUTYL PENTAERITHRITYL HYDROXYHYDROCINNAMATE, XANTHAN GUM, CITRIC ACID

15 SPF MINERAL SUN VEIL CREAM
NDC 64127-014-02

Ref. GV1725

ACTIVE INGREDIENTS

ZINC OXIDE 12.5%

INGREDIENTS

CYCLOPENTASILOXANE, CYCLOHEXASILOXANE, PEG-10 DIMETHICONE, POLYSILICONE-11, WATER/EAU, DIMETHICONE/DIVINYLDIMETHICONE/SILSESQUIOXANE CROSSPOLYMER, COPERNICIA CERIFERA (CARNAUBA) WAX, PPG-15 STEARYL ETHER, CETYL PEG/PPG-10/1 DIMETHICONE, GLYCERIN, BUTYLENE GLYCOL, CITRUS MEDICA LIMONIUM (LEMON) EXTRACT, FUMARIA OFFICINALIS EXTRACT, FUMARIC ACID, SODIUM BENZOTRIAZOLYL BUTYLPHENOL SULFONATE, BUTETH-3, TRIBUTYL CITRATE, TRIS (TETRAMETHYLHYDROXYPIPERIDINOL) CITRATE, ETHYLHEXYLGLYCERIN, CHLORPHENESIN, CASSIA ALATA (CANDLE TREE) LEAF EXTRACT, TOCOPHEROL (VITAMIN E)

MADE IN CANADA
® LABORATOIRES DERMO-COSMETIK INC.
68 STINSON, MONTREAL, QUEBEC, CANADA H4N 2E7

PRINCIPAL DISPLAY PANEL - Kit Carton

SYSTÈME ÉCLAIRCISSANT
PHYTOWHITE™
BRIGHTENING SYSTEM

Tous types de peau
All Skin Types

NDC 64127-084-01

SÉRUM
ANTI-TACHES
PHYTOWHITE™
DARK SPOT
SERUM
20 ml – 0.68 fl. oz.

CRÈME
PHYTOWHITE™
CREAM
50 ml – 1.7 fl. oz.

VOILE SOLAIRE
MINERAL
SUN VEIL
FPS 15 SPF
50 ml – Net wt. 1.7 oz.